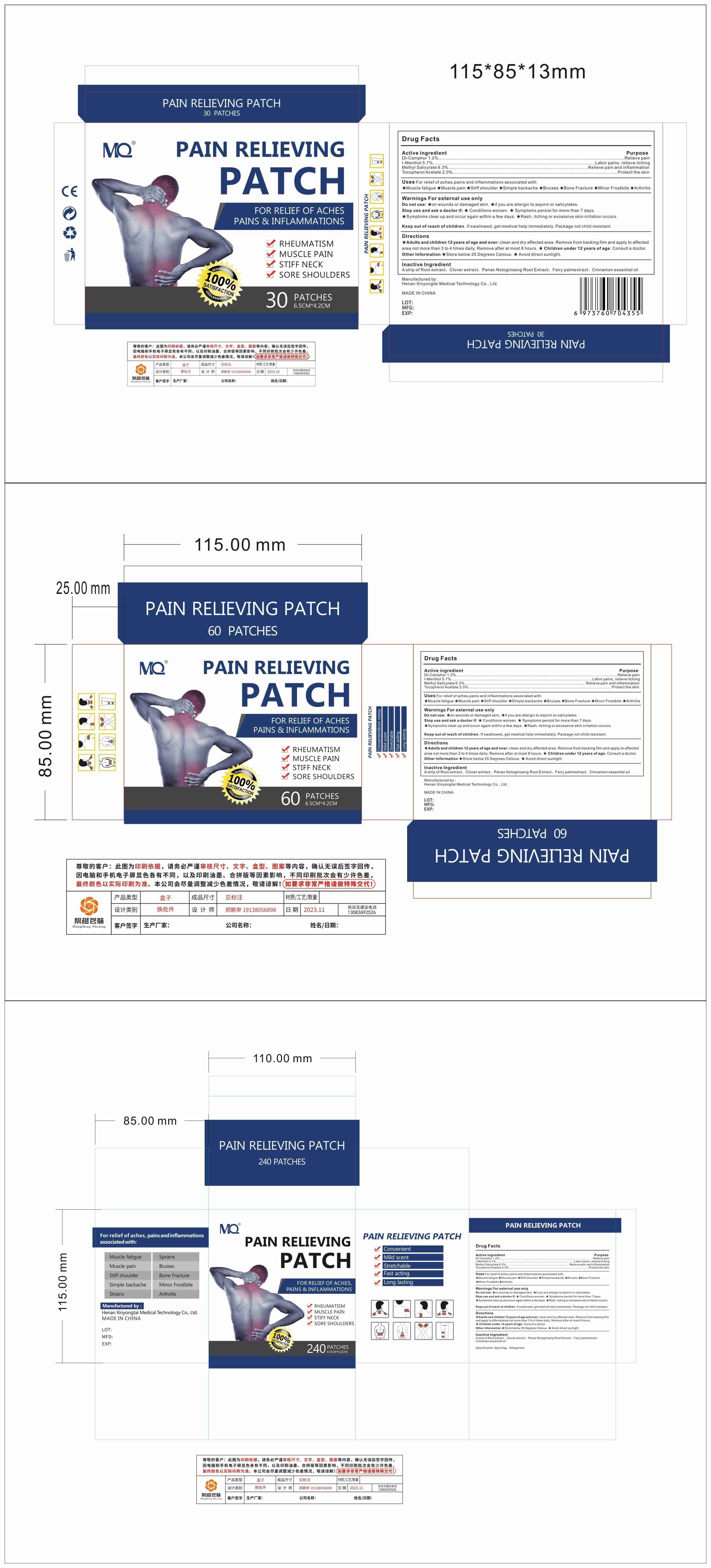 DRUG LABEL: MQ Pain Relieving Patch
NDC: 83781-006 | Form: PATCH
Manufacturer: Zhengzhou Miaoqi Pharmaceutical Technology Co., Ltd
Category: otc | Type: HUMAN OTC DRUG LABEL
Date: 20250324

ACTIVE INGREDIENTS: LEVOMENTHOL 5.7 g/100 1; METHYL SALICYLATE 6.3 g/100 1; CAMPHOR (SYNTHETIC) 1.2 g/100 1; .ALPHA.-TOCOPHEROL ACETATE 2 g/100 1
INACTIVE INGREDIENTS: GYNOSTEMMA PENTAPHYLLUM LEAF; FLEMINGIA PROSTRATA WHOLE; CINNAMON OIL; CLOVE; PANAX NOTOGINSENG ROOT

83781-006 Update V2

Active Ingredient

DL-Camphor 1.2%
L-Menthol 5.7%
Methyl Salicylate 6.3%
Tocopherol Acetate 2%

Purpose

Relieve pain
Labor pains, relieve itching
Relieve pain and inflammation
Protect the skin

Use

Uses For relief of aches,pains and inflammations associated with:
★Muscle fatigue

★Muscle pain

★Stiff shoulder

★Simple backache

★Bruises

★Bone Fracture

★Minor Frostbite

★Arthritis

Warnings

Warnings For external use only
Do not use:

★on wounds or damaged skin

★if you are allergic to aspirin or salicylates.
Stop use and ask a doctor if:

★ Conditions worsen.

★ Symptoms persist for more than 7 days.
★Symptoms clear up and occur again within a few days.

★Rash, itching or excessive skin irritation occurs.

Do not use

on wounds or damaged skin ★if you are allergic to aspirin or salicylates.

When Using

Clean, dry affected area. Remove from the backing film and apply to the affected area no more than 3 to 4 times a day. Remove after up to 8 hours.

Stop Use

Conditions worsen. ★ Symptoms persist for more than 7 days.
★Symptoms clear up and occur again within a few days.

★Rash, itching or excessive skin irritation occurs.

Ask Doctor

Children under 12 years of age

Keep Out Of Reach Of Children

Directions

clean and dry affected area. Remove from backing film and apply to affected area not more than 3 to 4 times daily. Remove after at most 8 hours.

Other information

★Store below 25 Degrees Celsius. ★ Avoid direct sunlight

Inactive ingredients

A strip of Root extract、Clover extract、Panax Notoginseng Root Extract、Fairy palm
extract、Cinnamon essential oil

Questions

mqupin86@gmail.com